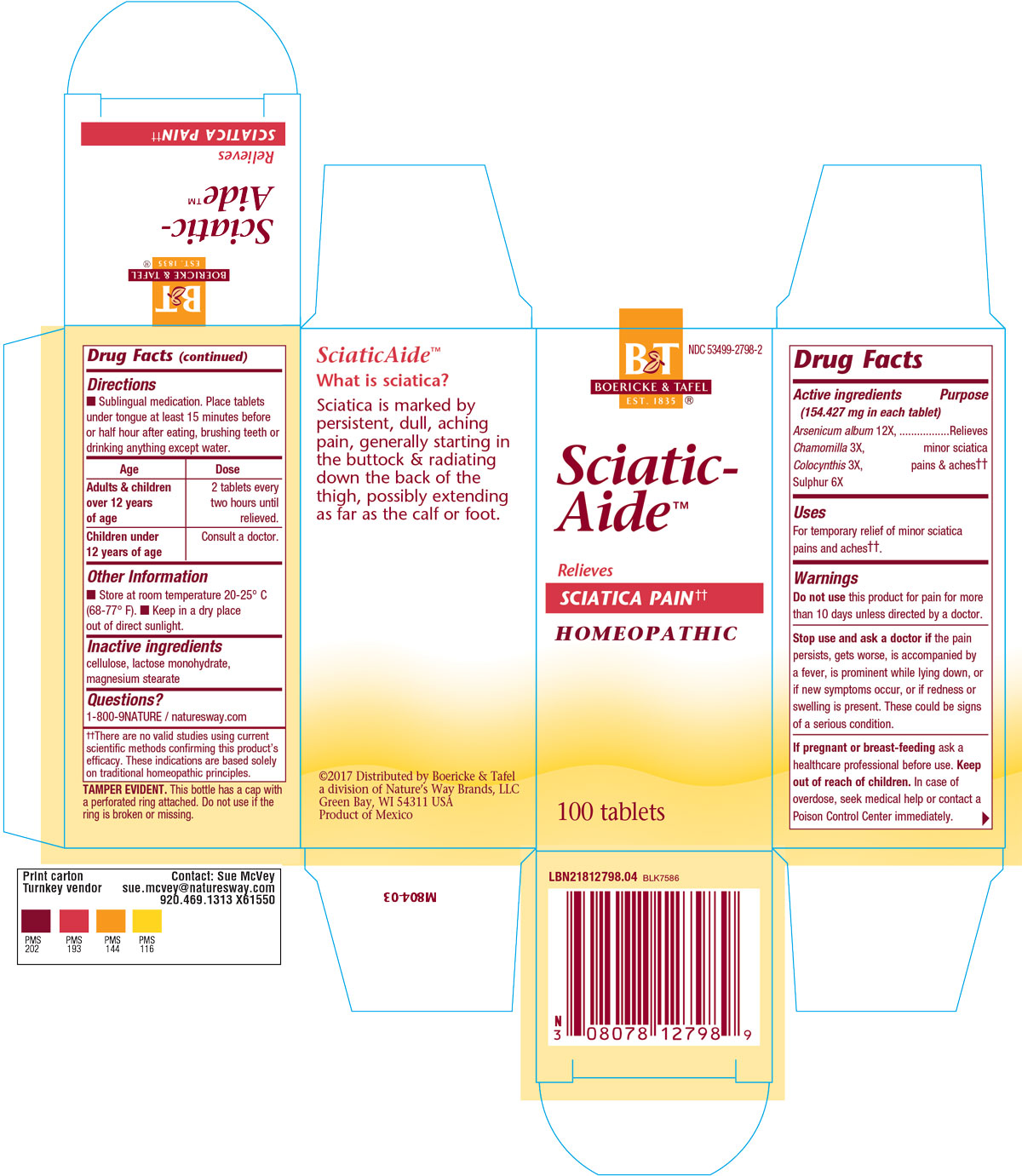 DRUG LABEL: SCIATIC AIDE
NDC: 53499-2798 | Form: TABLET
Manufacturer: Schwabe North America, Inc
Category: homeopathic | Type: HUMAN OTC DRUG LABEL
Date: 20220726

ACTIVE INGREDIENTS: ARSENIC TRIOXIDE 12 [hp_X]/1 1; CHAMOMILE 3 [hp_X]/1 1; CITRULLUS COLOCYNTHIS FRUIT PULP 3 [hp_X]/1 1; SULFUR 6 [hp_X]/1 1
INACTIVE INGREDIENTS: MAGNESIUM STEARATE; LACTOSE MONOHYDRATE; CELLULOSE, MICROCRYSTALLINE

Sciatic Aide

Active Ingredient

Arsenicum album 12X

Chamomilla 3X

Colocynthis 3X

Sulphur 6X

Inactive Ingredient

Cellulose

Lactose monohydrate

Magnesium stearate

Purpose

For the temporary relief of minor sciatica pains and aches.

Indications & Usage

For the temporary relief of minor sciatica pains and aches.

Dosage & Administration

Sublingual medication: Place tablets under tongue at least 15 mnutes before or half our after eating, brushing teeth, or drinking anything but water.
Adults and children 12 years of age: 2 tablets every two hours until relieved.
Children under 12 years of age: Consult a doctor.

Warning

Do not take this product for pain for more than 10 days unless directed by a doctor.

Stop Use

Stop use and ask a docitor if pain persists, gets worse, is accompanied by fever, is prominent while lying down, or if new symptoms occur, or redness or swelling is present.
These could be signs of a serious condition.

Pregnancy or Breast Feeding

If pregnant or breast-feeding, ask a healthcare professional before use.

Keep out of reach of children.

Overdose

In case of overdose, seek medical help or contact a Poison Control Center immediately.